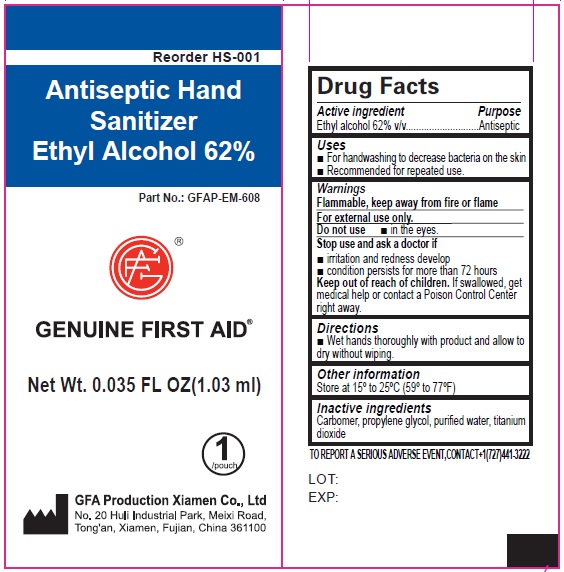 DRUG LABEL: Genuine First Aid Antiseptic Hand Sanitizer Ethyl Alcohol
NDC: 50814-056 | Form: CREAM
Manufacturer: GFA Production (Xiamen) Co., Ltd.
Category: otc | Type: HUMAN OTC DRUG LABEL
Date: 20241015

ACTIVE INGREDIENTS: ALCOHOL 0.62 mL/1 mL
INACTIVE INGREDIENTS: CARBOMER HOMOPOLYMER, UNSPECIFIED TYPE; PROPYLENE GLYCOL; WATER; TITANIUM DIOXIDE

Genuine First Aid Antiseptic Hand Sanitizer Ethyl Alcohol

Active ingredient

Ethyl alcohol, 62% v/v

Purpose

Antiseptic

Uses

- For handwashing to decrease bacteria on the skin
- Recommended for repeated use.

Warnings

Flammable, keep away from fire or flame

For external use only.

Do not use

- in the eyes.

Stop use and ask a doctor if

- irritation and redness develop.
- condition persists for more than 72 hours

Keep out of reach of children.

If swallowed, get medical help or contact a Poison Control Center right away.

Directions

- Wet hands thoroughly with product and allow to dry without wiping.

Other information

Store at 15°-25° C (59°-77° F)

Inactive ingredients

Carbomer, propylene glycol, purified water, titanium dioxide